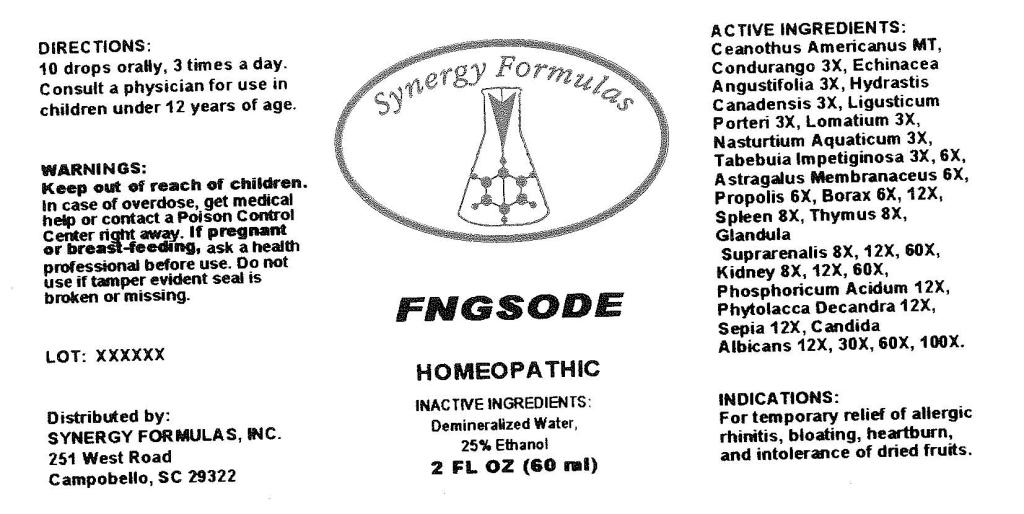 DRUG LABEL: Fngsode
NDC: 57520-0571 | Form: LIQUID
Manufacturer: Apotheca Company
Category: homeopathic | Type: HUMAN OTC DRUG LABEL
Date: 20110428

ACTIVE INGREDIENTS: CEANOTHUS AMERICANUS LEAF 1 [hp_X]/1 mL; MARSDENIA CONDURANGO BARK 3 [hp_X]/1 mL; ECHINACEA ANGUSTIFOLIA 3 [hp_X]/1 mL; GOLDENSEAL 3 [hp_X]/1 mL; LOMATIUM DISSECTUM ROOT 3 [hp_X]/1 mL; RORIPPA NASTURTIUM-AQUATICUM 3 [hp_X]/1 mL; TABEBUIA IMPETIGINOSA BARK 6 [hp_X]/1 mL; ASTRAGALUS PROPINQUUS ROOT 6 [hp_X]/1 mL; SODIUM BORATE 12 [hp_X]/1 mL; SUS SCROFA SPLEEN 8 [hp_X]/1 mL; SUS SCROFA THYMUS 8 [hp_X]/1 mL; SUS SCROFA ADRENAL GLAND 60 [hp_X]/1 mL; PORK KIDNEY 60 [hp_X]/1 mL; PHOSPHORIC ACID 12 [hp_X]/1 mL; PHYTOLACCA AMERICANA ROOT 12 [hp_X]/1 mL; SEPIA OFFICINALIS JUICE 12 [hp_X]/1 mL; CANDIDA ALBICANS 100 [hp_X]/1 mL; LIGUSTICUM PORTERI ROOT 3 [hp_X]/1 mL; PROPOLIS WAX 6 [hp_X]/1 mL
INACTIVE INGREDIENTS: WATER; ALCOHOL

Fngsode

ACTIVE INGREDIENT

ACTIVE INGREDIENTS: Ceanothus americanus 1X, Condurango 3X, Echinacea angustifolia 3X, Hydrastis canadensis 3X, Ligusticum porteri 3X, Lomatium 3X, Nasturtium aquaticum 3X, Tabebuia impetiginosa 3X, 6X, Astragalus membranaceus 6X, Propolis 6X, Borax 6X, 12X, Spleen 8X, Thymus 8X, Glandula suprarenalis 8X, 12X, 60X, Kidney 8X, 12X, 60X, Phosphoricum acidum 12X, Phytolacca decandra 12X, Sepia 12X, Candida albicans 12X, 30X, 60X, 100X.

PURPOSE

INDICATIONS: For temporary relief of allergic rhinitis, bloating, heartburn, and intolerance of dried fruits.

WARNINGS

WARNINGS: Keep out of reach of children. In case of overdose, get medical help or contact a Poison Control Center right away.

If pregnant or breast-feeding, ask a health professional before use.

Do not use if tamper evident seal is broken or missing.

DOSAGE AND ADMINISTRATION

DIRECTIONS: 10 drops orally, 3 times a day. Consult a physician for use in children under 12 years of age.

INACTIVE INGREDIENTS: Demineralized water, 25% Ethanol.

KEEP OUT OF REACH OF CHILDREN. In case of overdose, get medical help or contact a Poison Control Center right away.

INDICATIONS AND USAGE

INDICATIONS: For temporary relief of allergic rhinitis, bloating, heartburn, and intolerance of dried fruits.

QUESTIONS

Distributed by:

SYNERGY FORMULAS, INC.

251 West Road

Campobello, SC 29322

PACKAGE LABEL

SYNERGY FORMULAS

FNGSODE

HOMEOPATHIC

2 FL OZ (60 ml)